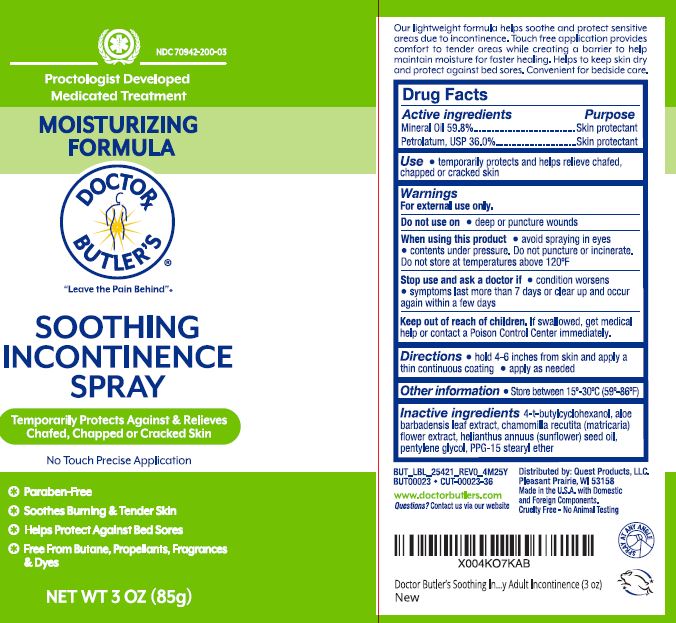 DRUG LABEL: Dr Butlers Soothing Incontinence
NDC: 70942-200 | Form: SPRAY
Manufacturer: Beyond Health PA
Category: otc | Type: HUMAN OTC DRUG LABEL
Date: 20250723

ACTIVE INGREDIENTS: MINERAL OIL 59.8 g/100 g; PETROLATUM 36 g/100 g
INACTIVE INGREDIENTS: 4-TERT-BUTYLCYCLOHEXANOL; SUNFLOWER OIL; PPG-15 STEARYL ETHER; ALOE; CHAMOMILE; PENTYLENE GLYCOL

Doctor Butler's Soothing Incontinence Spray

Active ingredients

Mineral Oil 59.8%

Petrolatum 36.0%

Purpose

Skin Protectant

Skin Protectant

Use

- temporarily protects and helps relieve chafed, chapped or cracked skin

Warnings

For external use only.

Do not use on

- deep or puncture wounds

When using this product

- avoid spraying in eyes
- contents under pressure. Do not puncture or incinerate. Do not store at temperatures above 120ºF

Stop use and ask a doctor if

- condition worsens
- symptoms last more than 7 days or clear up and occur again within a few days

Keep out of reach of children

If swallowed, get medical help or contact a Poison Control Center immediately.

Directions

- hold 4-6 inches from skin and apply a thin continuous coating
- apply as needed

Other Information

- Store between 15º-30º C (59º-86º F)

Inactive ingredients

4-t butylcyclohexanol

aloe barbadensis leaf extract

chamomilla recrutita (matricaria) flower extract

helianthus annuus (sunflower) seed oil

pentylene glycol

PPG-15 stearyl ether